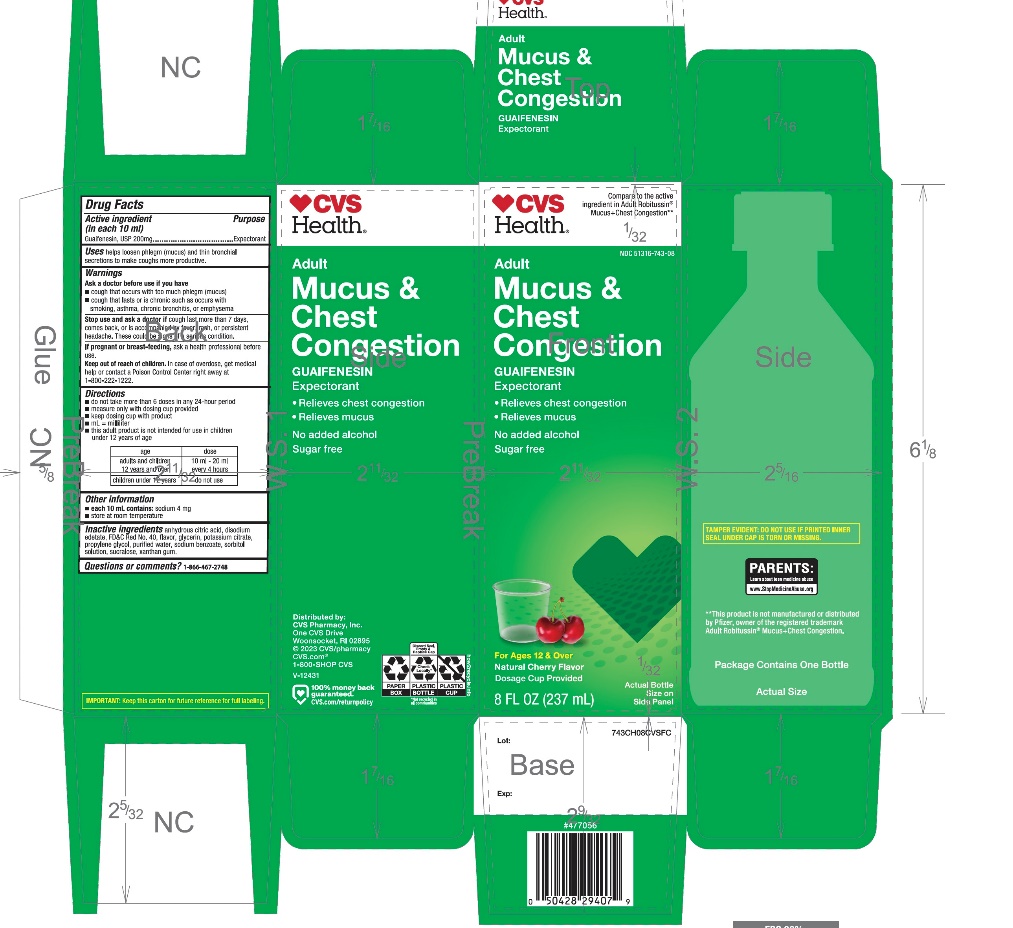 DRUG LABEL: CVS Adult Mucus

NDC: 51316-743 | Form: SYRUP
Manufacturer: CVS PHARMACY
Category: otc | Type: HUMAN OTC DRUG LABEL
Date: 20251210

ACTIVE INGREDIENTS: GUAIFENESIN 200 mg/10 mL
INACTIVE INGREDIENTS: ANHYDROUS CITRIC ACID; EDETATE DISODIUM; FD&C RED NO. 40; GLYCERIN; POTASSIUM CITRATE; PROPYLENE GLYCOL; WATER; SODIUM BENZOATE; SORBITOL; SUCRALOSE; XANTHAN GUM

CVS Adult Mucus + Chest Congestion Drug Facts

Active ingredient (in each 10 mL)

Guaifenesin, USP 200 mg

Purpose

Expectorant

Uses

helps loosen phlegm (mucus) and thin bronchial secretions to make coughs more productive

Warnings

Ask a doctor before use if you have

- cough that occurs with too much phlegm (mucus)
- cough that lasts or is chronic such as occurs with smoking, asthma, chronic bronchitis, or emphysema

Stop use and ask a doctor if

cough last for more than 7 days, comes back, or is accompanied by fever, rash, or persistent headache. A persistent cough may be a sign of a serious condition.

If pregnant or breast-feeding,

ask a health professional before use.

Keep out of reach of children.

In case of overdose, get medical help or contact a Poison Control Center right away at (1-800-222-1222).

Directions

- do not take more than 6 doses in any 24-hour period
- measure only with dosing cup provided
- keep dosing cup with product
- mL = milliliter
- this adult product is not intended for use in children under 12 years of age

age | dose
adults and children 12 years and over | 10 ml – 20 ml every 4 hours
children under 12 years | do not use

Other information

- each 10 mL contains:sodium 4 mg
- store at room temperature

Inactive ingredients

anhydrous citric acid, disodium edetate, FD&C red no. 40, flavor, glycerin, potassium citrate, propylene glycol, purified water, sodium benzoate, sorbitol, sucralose, xanthan gum.

Principal Display Panel

NDC# 51316-743-08

Compare to the active ingredient in Adult Robitussin Mucus + Chest Congestion*

Adult

Mucus+Chest

Congestion

Guaifenesin (Expectorant)

Relieves:

- Mucus
- Chest congestion

Sugar-Free

No Added Alcohol

Use Dosage Cup Included

Natural Cherry Flavor

For Ages 12 & Over

8 FL OZ (237 mL)

IMPORTANT:Keep this carton for future reference on full labeling.

*This product is not manufactured or distributed by GSK Consumer Healthcare, owner of the registered trademark Adult Robitussin Mucus + Chest Congestion.